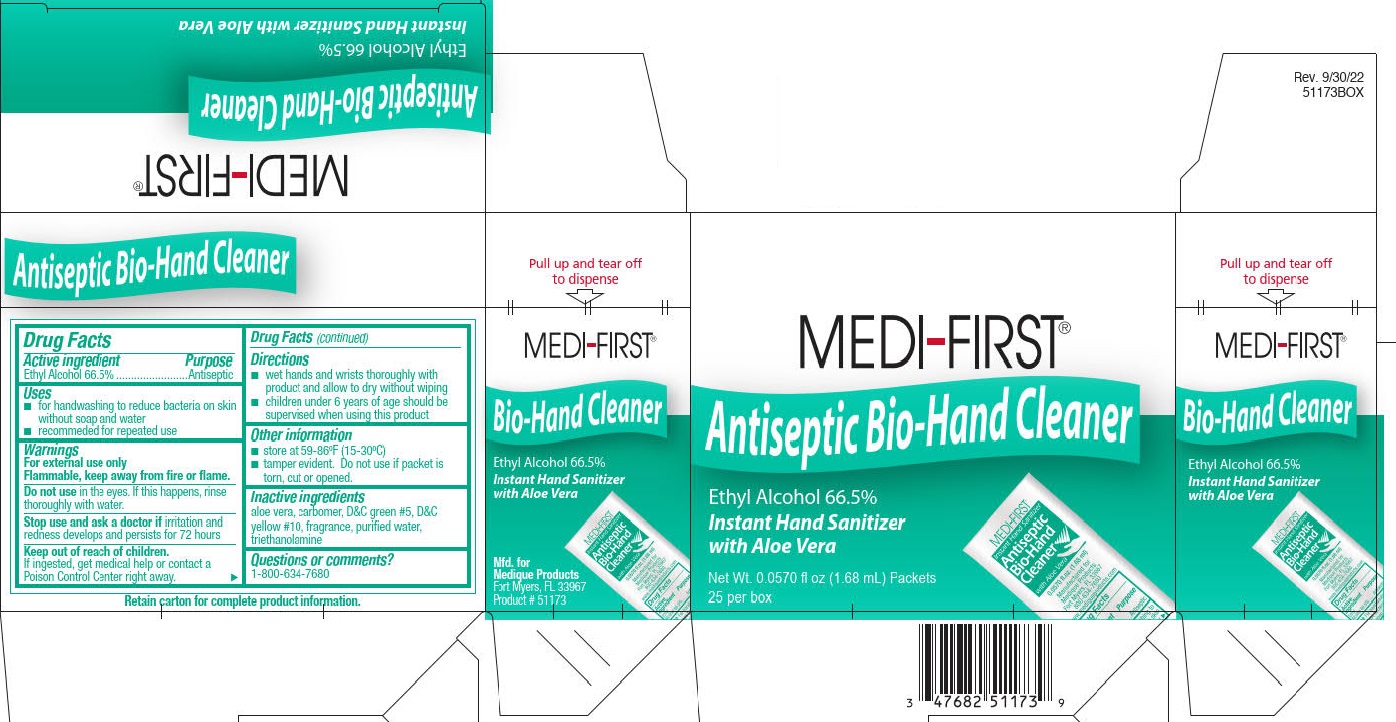 DRUG LABEL: Hand Sanitizer
NDC: 47682-511 | Form: GEL
Manufacturer: Unifirst First Aid Corporation
Category: otc | Type: HUMAN OTC DRUG LABEL
Date: 20250909

ACTIVE INGREDIENTS: ALCOHOL 540.26 g/1 L
INACTIVE INGREDIENTS: ALOE; CARBOMER INTERPOLYMER TYPE A (ALLYL SUCROSE CROSSLINKED); D&C GREEN NO. 5; D&C YELLOW NO. 10; WATER; TROLAMINE

Medi-First Antiseptic Bio-Hand Cleaner

Drug Facts

Active ingredient

Ethyl Alcohol 66.5%

Purpose

Antiseptic

Uses

- for handwashing to reduce bacteria on skinwithout soap and water
- recommended for repeated use

Warnings

Flammable. keep away from fire of flame.

For external use only.

Do not use in the eyes. If this happens, rinse thoroughly with water.

Stop use and ask doctor if irritation and redness develops and persists for 72 hours

Keep out of reach of children. If ingested, get medical help or contact a Poison Control Center right away.

Directions

- wet hands and wrists thoroughly with product and allow to dry without wiping
- children under 6 years of age should be supervised when using this product

Other information

- store at 59-86ºF (15-30ºC)
- tamper evident. Do not use if packet is torn, cut or opened.

INACTIVE INGREDIENT

Inactive ingredients aloe vera, carbomer, D&C green #5, D&C yellow #10, fragrance, purified water, triethanolamine

Questions or comments? 1-800-634-7680

MEDI-FIRST Antiseptic Bio-Hand Cleaner Label

MEDI-FIRST®

Antiseptic Bio Hand Cleaner

Ethyl Alcohol 66.5%

Instant Hand Sanitizer

with Aloe Vera

Mfd. for Medique Products

Fort Myers, FL 33967

Product # 51173

0.0570 fl. oz. (1.68 ml) Packets

25 per box